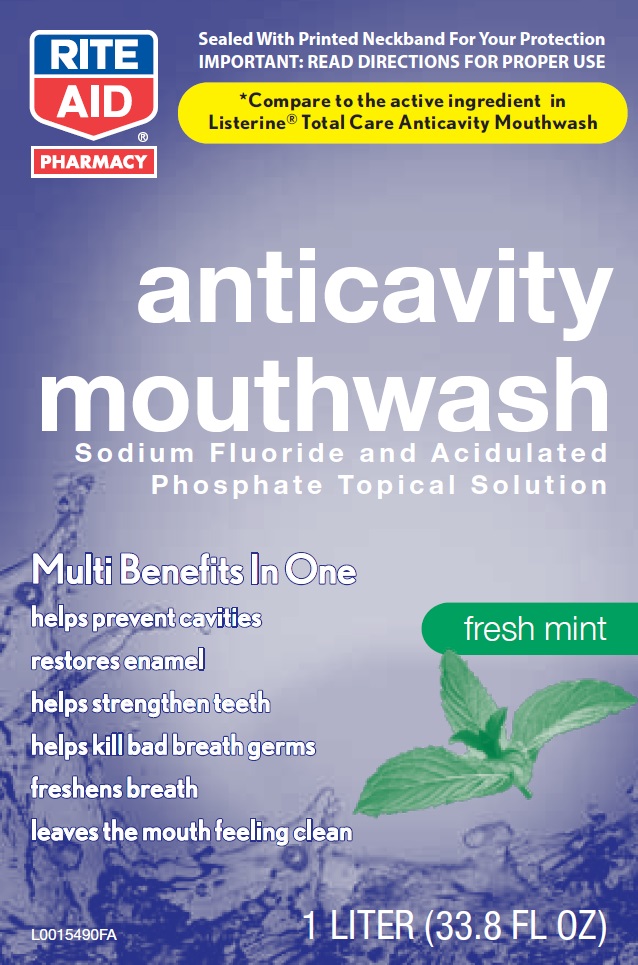 DRUG LABEL: Anticavity Fluoride Rinse
NDC: 11822-3705 | Form: MOUTHWASH
Manufacturer: Rite Aid
Category: otc | Type: HUMAN OTC DRUG LABEL
Date: 20160226

ACTIVE INGREDIENTS: SODIUM FLUORIDE 0.1 mg/1 mL
INACTIVE INGREDIENTS: WATER; ALCOHOL; SORBITOL; POLOXAMER 407; SODIUM LAURYL SULFATE; EUCALYPTOL; METHYL SALICYLATE; THYMOL; PHOSPHORIC ACID; sucralose; MENTHOL; SODIUM PHOSPHATE, DIBASIC, ANHYDROUS; FD&C RED NO. 40; FD&C BLUE NO. 1

Drug Facts

Active ingredient

Sodium fluoride 0.0221% (0.01% w/v fluoride ion)

Purpose

Anticavity

Use

aids in the prevention of dental cavities

Warning

Keep out of reach of children. If more than used for rinsing is accidentally swallowed, get medical help or contact a Poison Control Center right away.

Directions

Adults and children 12 years of age and older:

- use twice daily after brushing your teeth with toothpaste
- vigorously swish 10 mL (2 teaspoonfuls) of rinse between your teeth for 1 minute and then spit out
- do not swallow the rinse
- do not eat or drink for 30 minutes after rinsing
- instruct children under 12 years of age in good rinsing habits (to minimize swallowing)
- supervise children as necessary until capable of using without supervision
- children under 12 years of age: consult a dentist or doctor

Other information

- store at controlled room temperature 20⁰ -25⁰ C (68⁰ - 77⁰ F)
- cold weather may temporarily cloud this product

Inactive ingredients

water, alcohol (21.6%), sorbitol, poloxamer 407, sodium lauryl sulfate, eucalyptol, flavor, methyl salicylate, thymol, phosphoric acid, sucralose, menthol, disosium phosphate, red 40, blue 1

*This product is not manufactured or distributed by Johnson + Johnson Healthcare Products, distributor of Listerine Total Care Anticavity Mouthwash

DISTRIBUTED BY:

RITE AID

3O Hunter Lane, Camp Hill, PA 17011

DSP-TN-1500

DSP-MO-34

SDS-TN-15012

Principal Display Panel

RITE AID PHARMACY

Sealed With Printed Neckband For Your Protection

IMPORTANT: READ DIRECTIONS FOR PROPER USE

*Compare to the active ingredient in Listerine Total Care Anticavity Mouthwash

Anticavity Mouthwash

Sodium Fluoride and Acidulated Phosphate Topical Solution

fresh mint

helps prevent cavities

restores enamel

helps strengthen teeth

helps kill bad breath germs

leaves the mouth feeling clean

1 LITER (33.8 FL OZ)